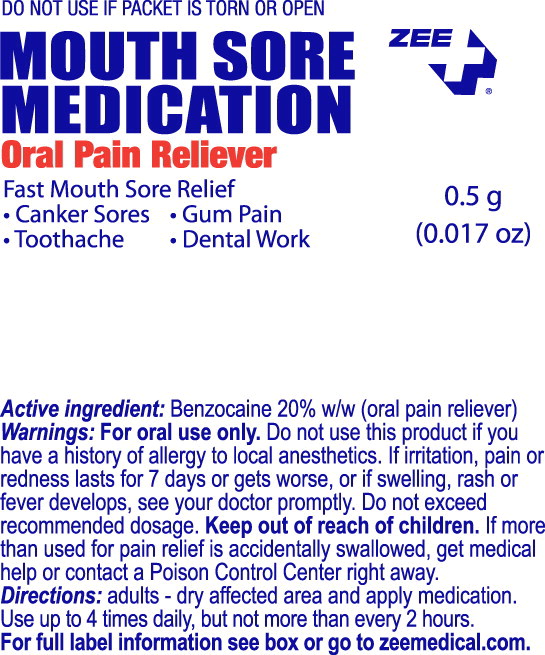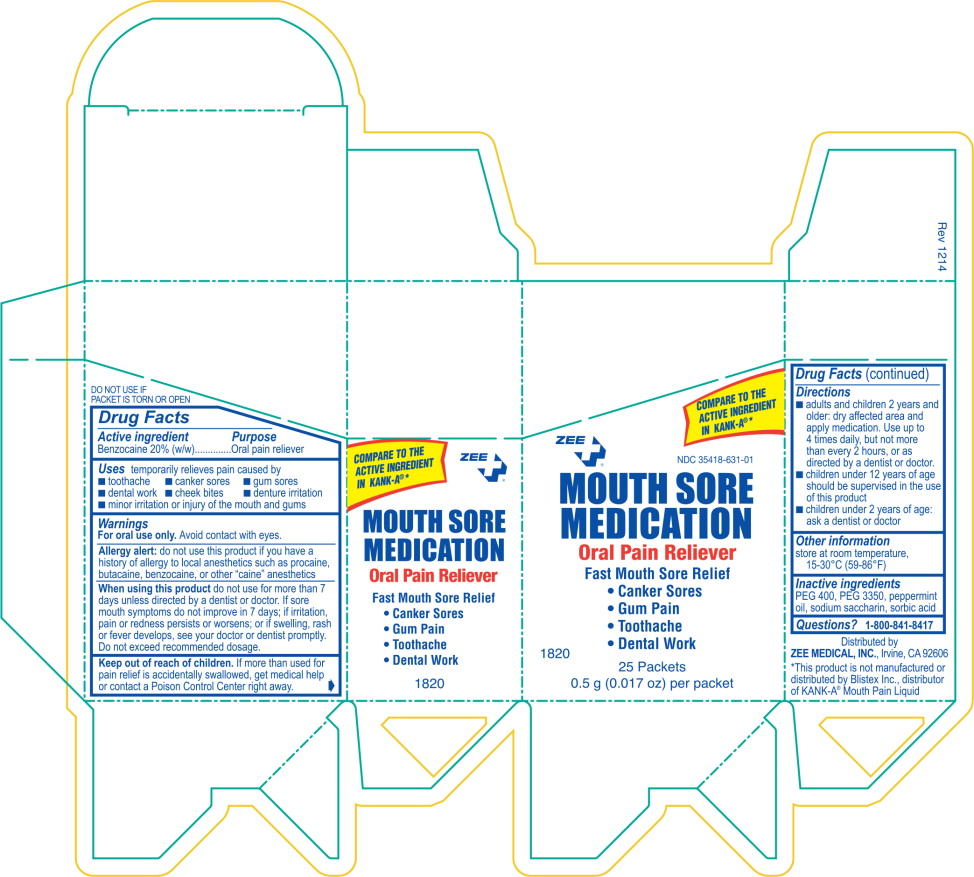 DRUG LABEL: Mouth Sore Medication
NDC: 35418-631 | Form: LIQUID
Manufacturer: Zee Medical
Category: otc | Type: HUMAN OTC DRUG LABEL
Date: 20140623

ACTIVE INGREDIENTS: benzocaine 200 mg/1 g
INACTIVE INGREDIENTS: polyethylene glycol 400; polyethylene glycol 3350; peppermint oil; saccharin sodium dihydrate; sorbic acid

COMPARE TO THE ACTIVE INGREDIENT IN KANK-A®

ZEE MOUTH SORE MEDICATION

ORAL PAIN RELIEVER

Fast Mouth Sore Relief

- Canker sores
- Gum Pain
- Toothache
- Dental Work

25 Packets

0.5g (0.017 oz) per packet

DO NOT USE IF PACKET IS TORN OR OPEN

Drug Facts

Active ingredient

Benzocaine 20% (w/w)

Purpose

Oral pain reliever

Uses

temporarily relieves pain caused by

- toothache
- canker sores
- gum sores
- dental work
- cheek bites
- denture irritation
- minor irritation or injury of the mouth and gums

Warnings

For oral use only. Avoid contact with eyes.

Allergy alert: do not use this product if you have a history of allergy to local anesthetics such as procaine, butacaine, benzocaine, or other “caine” anesthetics

When using this product do not use for more than 7 days unless directed by a dentist or doctor. If sore mouth symptoms do not improve e in 7 days; if irritation, pain or redness persists or worsens; or if swelling, rash or fever develops, see your doctor or dentist promptly. Do not exceed recommended dosage.

Keep out of reach of children. If more than used for pain relief is accidentally swallowed, get medical help or contact a Poison Control Center right away.

Directions

- adults and children 2 years and older: dry affected area and apply medication. Use up to 4 times daily, but not more than every 2 hours, or as directed by a dentist or doctor.
- children under 12 years of age should be supervised in the use of this product
- children under 2 years of age: ask a dentist or doctor

Inactive ingredients

PEG 400, PEG 3350, peppermint oil, sodium saccharin, sorbic acid

Questions?

1-800-841-8417

Distributed by
Zee Medical, Inc., Irvine,CA 92606
This product is not manufactured or distributed by Blistex, Inc., distributor of KANK-A® Mouth Pain Liquid

PRINCIPAL DISPLAY PANEL – packet label

DO NOT USE IF PACKET IS TORN OR OPEN

MOUTH SORE ZEE

MEDICATION

Oral Pain Reliever

Fast Mouth Sore Relief

- Canker sores
- Gum Pain
- Toothache
- Dental Work

5g (0.017 oz)

PRINCIPAL DISPLAY PANEL – Carton label

NDC 35418-631-01

COMPARE TO THE ACTIVE INGREDIENT IN KANK-A®*

ZEE MOUTH SORE MEDICATION

ORAL PAIN RELIEVER

Fast Mouth Sore Relief

- Canker sores
- Gum Pain
- Toothache
- Dental Work

25 Packets

0.5g (0.017 oz) per packet